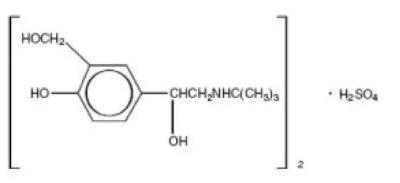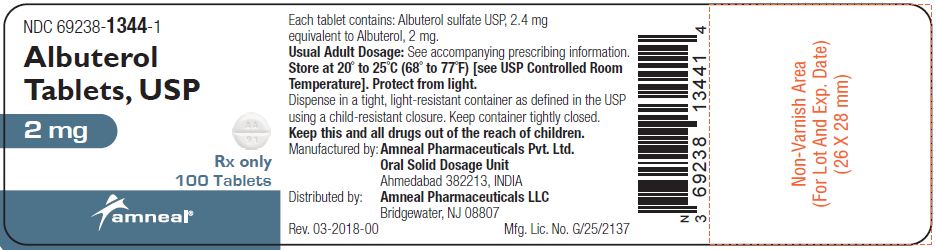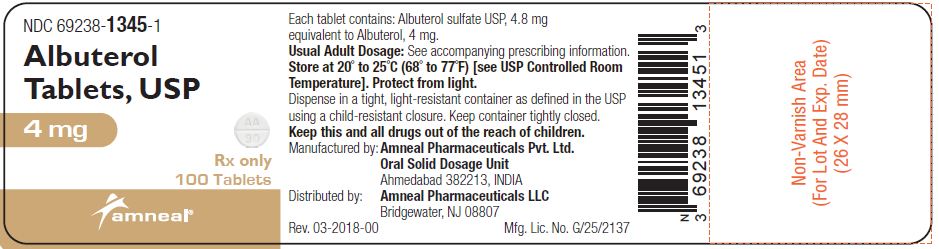 DRUG LABEL: Albuterol
NDC: 69238-1344 | Form: TABLET
Manufacturer: Amneal Pharmaceuticals NY LLC
Category: prescription | Type: HUMAN PRESCRIPTION DRUG LABEL
Date: 20241209

ACTIVE INGREDIENTS: ALBUTEROL SULFATE 2 mg/1 1
INACTIVE INGREDIENTS: LACTOSE MONOHYDRATE; MAGNESIUM STEARATE; STARCH, CORN; SODIUM LAURYL SULFATE

Albuterol Tablets, USP
(2 mg and 4 mg)
Rx only

DESCRIPTION

Albuterol tablets, USP contain albuterol sulfate, USP, the racemic form of albuterol and a relatively selective beta2 -adrenergic bronchodilator. Albuterol sulfate has the chemical name α^1-[(tert-Butylamino) methyl]- 4-hydroxy-m-xylene-α,α'-diol sulfate (2:1) (salt) and the following structural formula:

The molecular weight of albuterol sulfate is 576.71, and the molecular formula is (C13H21NO3)2 •H2SO4.

Albuterol sulfate, USP is a white or practically white powder, freely soluble in water and slightly soluble in ethanol. The World Health Organization recommended name for albuterol base is salbutamol.

Each albuterol tablet, USP for oral administration contains 2 mg or 4 mg of albuterol as 2.4 mg or 4.8 mg of albuterol sulfate, USP respectively.

Each tablet also contains the following inactive ingredients: lactose monohydrate, magnesium stearate, pregelatinized (corn) starch and sodium lauryl sulfate.

CLINICAL PHARMACOLOGY

The primary action of beta-adrenergic agonist drugs, including albuterol, is to stimulate adenyl cyclase, the enzyme which catalyzes the formation of cyclic-3',5'- adenosine monophosphate (cyclic AMP) from adenosine triphosphate (ATP) in beta-adrenergic cells. The cyclic AMP thus formed mediates the cellular responses. Increased cyclic AMP levels are associated with relaxation of bronchial smooth muscle and inhibition of release of mediators of immediate hypersensitivity from cells, especially from mast cells.

In vitro studies and in vivo pharmacologic studies have demonstrated that albuterol has a preferential effect on beta2 -adrenergic receptors compared with isoproterenol. While it is recognized that beta2- adrenergic receptors are the predominant receptors in bronchial smooth muscle, data indicate that there is a population of beta2-receptors in the human heart existing in a concentration between 10% and 50%. The precise function of these receptors has not been established.

In controlled clinical trials, albuterol has been shown to have more effect on the respiratory tract, in the form of bronchial smooth muscle relaxation, than isoproterenol at comparable doses while producing fewer cardiovascular effects. Controlled clinical studies and other clinical experience have shown that inhaled albuterol, like other beta-adrenergic agonist drugs, can produce a significant cardiovascular effect in some patients, as measured by pulse rate, blood pressure, symptoms, and/or ECG changes.

Albuterol is longer acting than isoproterenol in most patients by any route of administration because it is not a substrate for the cellular uptake processes for catecholamines nor for catechol-O-methyl transferase.

Preclinical

Intravenous studies in rats with albuterol sulfate have demonstrated that albuterol crosses the blood-brain barrier and reaches brain concentrations amounting to approximately 5% of the plasma concentrations. In structures outside the blood-brain barrier (pineal and pituitary glands), albuterol concentrations were found to be 100 times those in the whole brain.

Studies in laboratory animals (minipigs, rodents, and dogs) have demonstrated the occurrence of cardiac arrhythmias and sudden death (with histologic evidence of myocardial necrosis) when beta-agonists and methylxanthines are administered concurrently. The clinical significance of these findings is unknown.

Pharmacokinetics

Albuterol is rapidly and well absorbed following oral administration.

In studies involving normal volunteers, the mean steady-state peak and trough plasm levels of albuterol were 6.7 ng/mL and 3.8 ng/mL, respectively, following dosing with a 2 mg albuterol tablet every 6 hours and 14.8 ng/mL and 8.6 ng/mL, respectively following dosing with a 4 mg albuterol tablet every 6 hours. Maximum albuterol plasma levels are usually obtained between 2 and 3 hours after dosing, and the elimination half-life is 5 to 6 hours. These data indicate that albuterol administered orally is dose proportional and exhibits dose independent pharmacokinetics.

Albuterol extended-release tablets have been formulated to provide a duration of action of up to 12 hours. In studies conducted in normal volunteers, the mean steady-state peak and trough plasma levels of albuterol were 6.5 ng/mL and 3.0 ng/mL, respectively, following dosing with a 4 mg albuterol extended-release tablet every 12 hours. In addition, it has been shown that administration of a 4 mg albuterol extended-release tablets every 12 hours, and a 2 mg albuterol tablet every 6 hours for 5 days gave comparable peak albuterol levels and similar extent of absorption at steady state.

In other studies, the analysis of urine samples of patients given tritiated albuterol (4 mg to 10 mg) orally showed that 65% to 90% of the dose was excreted over 3 days, with the majority of the dose being excreted within the first 24 hours. Sixty percent of this radioactivity was shown to be the metabolite. Feces collected over this period contained 4% of the administered dose.

Clinical Trials

In controlled clinical trials in patients with asthma, the onset of improvement in pulmonary function, as measured by maximum midexpiratory flow rate (MMEF), was noted within 30 minutes after a dose of albuterol tablets, with peak improvement occurring between 2 and 3 hours. In controlled clinical trials in which measurements were conducted for 6 hours, significant clinical improvement in pulmonary function (defined as maintaining a 15% or more increase in FEV1 and a 20% or more increase in MMEF over baseline values) was observed in 60% of patients at 4 hours and in 40% at 6 hours. In other single-dose, controlled clinical trials, clinically significant improvement was observed in at least 40% of the patients at 8 hours with the 4 mg albuterol tablet. No decrease in the effectiveness of albuterol tablets has been reported in patients who received long-term treatment with the drug in uncontrolled studies for periods up to 6 months.

In another controlled clinical study in asthmatic patients, it has been demonstrated that the initiation of therapy with either the 4 mg albuterol extended-release tablet dosed every 12 hours, or the 2 mg albuterol tablet dosed every 6 hours, achieve therapeutically comparable effects.

INDICATIONS AND USAGE

Albuterol tablets, USP are indicated for the relief of bronchospasm in adults and children 6 years of age and older with reversible obstructive airway disease.

CONTRAINDICATIONS

Albuterol tablets are contraindicated in patients with a history of hypersensitivity to albuterol, or any of their components.

WARNINGS

Paradoxical Bronchospasm

Albuterol tablets can produce paradoxical bronchospasm, which may be life threatening. If paradoxical bronchospasm occurs, albuterol tablets should be discontinued immediately and alternative therapy instituted.

Deterioration of Asthma

Asthma may deteriorate acutely over a period of hours, or chronically over several days or longer. If the patient needs more doses of albuterol tablets than usual, this may be a marker of destabilization of asthma and requires re-evaluation of the patient and the treatment regimen, giving special consideration to the possible need for anti-inflammatory treatment, e.g., corticosteroids.

Use of Anti-Inflammatory Agents

The use of beta-adrenergic agonist bronchodilators alone may not be adequate to control asthma in many patients. Early consideration should be given to adding anti-inflammatory agents, e.g., corticosteroids.

Cardiovascular Effects

Albuterol tablets, like all other beta-adrenergic agonists, can produce a clinically significant cardiovascular effect in some patients as measured by pulse rate, blood pressure, and/or symptoms. Although such effects are uncommon after administration of albuterol tablets at recommended doses, if they occur, the drug may need to be discontinued. In addition, beta-agonists have been reported to produce electrocardiogram (ECG) changes, such as flattening of the T wave, prolongation of the QTc interval, and ST segment depression. The clinical significance of these findings is unknown. Therefore, albuterol tablets, like all sympathomimetic amines, should be used with caution in patients with cardiovascular disorders, especially coronary insufficiency, cardiac arrhythmias, and hypertension.

Immediate Hypersensitivity Reactions

Immediate hypersensitivity reactions may occur after administration of albuterol, as demonstrated by rare cases of urticaria, angioedema, rash, bronchospasm, anaphylaxis and oropharyngeal edema.

Rarely, erythema multiforme and Stevens-Johnson syndrome have been associated with the administration of oral albuterol sulfate in children.

PRECAUTIONS

General

Albuterol, as with all sympathomimetic amines, should be used with caution in patients with cardiovascular disorders, especially coronary insufficiency, cardiac arrhythmias, and hypertension; in patients with convulsive disorders, hyperthyroidism, or diabetes mellitus; and in patients who are unusually responsive to sympathomimetic amines. Clinically significant changes in systolic and diastolic blood pressure have been seen and could be expected to occur in some patients after use of any beta-adrenergic bronchodilator.

Large doses of intravenous albuterol have been reported to aggravate preexisting diabetes mellitus and ketoacidosis. As with other beta-agonists, albuterol may produce significant hypokalemia in some patients, possibly through intracellular shunting, which has the potential to produce adverse cardiovascular effects. The decrease is usually transient, not requiring supplementation.

Information for Patients

Patients being treated with albuterol tablets should receive the following information and instructions. This information is intended to aid in the safe and effective use of this medication. It is not a disclosure of all possible adverse or intended effects.

The action of albuterol tablets may last up to 6 to 8 hours or longer. Albuterol tablets should not be taken more frequently than recommended. Do not increase the dose or frequency of albuterol tablets without consulting your physician. If you find that treatment with albuterol tablets becomes less effective for symptomatic relief, your symptoms get worse, and/or you need to take the product more frequently than usual, you should seek medical attention immediately. While you are taking albuterol tablets, other inhaled drugs and asthma medications should be taken only as directed by your physician. Common adverse effects include palpitations, chest pain, rapid heart rate, and tremor or nervousness. If you are pregnant or nursing, contact your physician about the use of albuterol tablets. Effective and safe use of albuterol tablets includes an understanding of the way that it should be administered.

Drug Interactions

The concomitant use of albuterol tablets and other oral sympathomimetic agents is not recommended since such combined use may lead to deleterious cardiovascular effects. This recommendation does not preclude the judicious use of an aerosol bronchodilator of the adrenergic stimulant type in patients receiving albuterol tablets. Such concomitant use, however, should be individualized and not given on a routine basis. If regular co-administration is required, then alternative therapy should be considered.

Beta-Blockers

Beta-adrenergic receptor blocking agents not only block the pulmonary effect of beta-agonists, such as albuterol tablets, but may produce severe bronchospasm in asthmatic patients. Therefore, patients with asthma should not normally be treated with beta-blockers. However, under certain circumstances, e.g., as prophylaxis after myocardial infarction, there may be no acceptable alternatives to the use of beta-adrenergic blocking agents in patients with asthma. In this setting, cardioselective beta-blockers could be considered, although they should be administered with caution.

Diuretics

The ECG changes and/or hypokalemia that may result from the administration of non-potassium-sparing diuretics (such as loop or thiazide diuretics) can be acutely worsened by beta-agonists, especially when the recommended dose of the beta-agonist is exceeded. Although the clinical significance of these effects is not known, caution is advised in the co-administration of beta-agonists with nonpotassium-sparing diuretics.

Digoxin

Mean decreases of 16% to 22% in serum digoxin levels were demonstrated after single-dose intravenous and oral administration of albuterol, respectively, to normal volunteers who had received digoxin for 10 days. The clinical significance of these findings for patients with obstructive airway disease who are receiving albuterol and digoxin on a chronic basis is unclear. Nevertheless, it would be prudent to carefully evaluate the serum digoxin levels in patients who are currently receiving digoxin and albuterol.

Monoamine Oxidase Inhibitors or Tricyclic Antidepressants

Albuterol should be administered with extreme caution to patients being treated with monoamine oxidase inhibitors or tricyclic antidepressants, or within 2 weeks of discontinuation of such agents, because the action of albuterol on the vascular system may be potentiated.

Carcinogenesis, Mutagenesis, Impairment of Fertility

In a 2-year study in Sprague-Dawley rats, albuterol sulfate caused a significant dose-related increase in the incidence of benign leiomyomas of the mesovarium at and above dietary doses of 2 mg/kg (corresponding to less than the maximum recommended daily oral dose for adults and children on an mg/m^2 basis). In another study this effect was blocked by the co-administration of propranolol, a non-selective beta-adrenergic antagonist.

In an 18-month study in CD-1 mice albuterol sulfate showed no evidence of tumorigenicity at dietary doses of up to 500 mg/kg, (approximately 65 times the maximum recommended daily oral dose for adults on an mg/m^2 basis, or, approximately 50 times the maximum recommended daily oral dose for children on an mg/m^2 basis). In a 22-month study in the Golden hamster, albuterol sulfate showed no evidence of tumorigenicity at dietary doses of up to 50 mg/kg, (approximately 8 times the maximum recommended daily oral dose for adults and children on an mg/m^2 basis).

Albuterol sulfate was not mutagenic in the Ames test with or without metabolic activation using tester strains S. typhimurium TA1537, TA1538, and TA98 or E. Coli WP2, WP2uvrA, and WP67. No forward mutation was seen in yeast strain S. cerevisiae S9 nor any mitotic gene conversion in yeast strain S. cerevisiae JD1 with or without metabolic activation. Fluctuation assays in S. typhimurium TA98 and E. Coli WP2, both with metabolic activation, were negative. Albuterol sulfate was not clastogenic in a human peripheral lymphocyte assay or in an AH1 strain mouse micronucleus assay

Reproduction studies in rats demonstrated no evidence of impaired fertility at oral doses up to 50 mg/kg (approximately 15 times the maximum recommended daily oral dose for adults on an mg/m^2 basis).

Pregnancy

Teratogenic Effects

Pregnancy Category C

Albuterol has been shown to be teratogenic in mice. A study in CD-1 mice at subcutaneous (sc) doses at and above 0.25 mg/kg (corresponding to less than the maximum recommended daily oral dose for adults on an mg/m^2 basis), induced cleft palate formation in 5 of 111 (4.5%) fetuses. At an sc dose of 2.5 mg/kg (corresponding to less than the maximum recommended daily oral dose for adults on an mg/m^2 basis) albuterol sulfate induced cleft palate formation in 10 of 108 (9.3%) fetuses. The drug did not induce cleft palate formation when administered at an sc dose, 0.025 mg/kg (significantly less than the maximum recommended daily oral dose for adults on an mg/m^2 basis). Cleft palate also occurred in 22 of 72 (30.5%) fetuses from females treated with 2.5 mg/kg of isoproterenol (positive control) subcutaneously.

A reproduction study in Stride Dutch rabbits revealed cranioschisis in 7 of 19 (37%) fetuses when albuterol was administered orally at a dose of 50 mg/kg (approximately 25 times the maximum recommended daily oral dose for adults on an mg/m^2 basis).

Studies in pregnant rats with tritiated albuterol demonstrated that approximately 10% of the circulating maternal drug is transferred to the fetus. Disposition in the fetal lungs is comparable to maternal lungs, but fetal liver disposition is 1% of the maternal liver levels.

There are no adequate and well-controlled studies in pregnant women. Because animal reproduction studies are not always predictive of human response, albuterol should be used during pregnancy only if the potential benefit justifies the potential risk to the fetus.

During worldwide marketing experience, various congenital anomalies, including cleft palate and limb defects, have been reported in the offspring of patients being treated with albuterol.

Some of the mothers were taking multiple medications during their pregnancies. Because no consistent pattern of defects can be discerned, a relationship between albuterol use and congenital anomalies has not been established.

Labor and Delivery

Use in Labor

Because of the potential for beta-agonist interference with uterine contractility, use of albuterol tablets for relief of bronchospasm during labor should be restricted to those patients in whom the benefits clearly outweigh the risk.

Tocolysis

Albuterol has not been approved for the management of preterm labor. The benefit/risk ratio when albuterol is administered for tocolysis has not been established. Serious adverse reactions, including maternal pulmonary edema, have been reported during or following treatment of premature labor with beta2-agonists, including albuterol.

Nursing Mothers

It is not known whether this drug is excreted in human milk. Because of the potential for tumorigenicity shown for albuterol in some animal studies, a decision should be made whether to discontinue nursing or to discontinue the drug, taking into account the importance of the drug to the mother.

Pediatric Use

Safety and effectiveness of albuterol tablets and albuterol extended-release tablets have been established in pediatric patients 6 years of age and older. Use of albuterol extended-release tablets in these age groups is supported by evidence from adequate and well-controlled studies of albuterol extended-release tablets in adults: the likelihood that the disease course, pathophysiology, and the drug’s effect in pediatric and adult patients are substantially similar,; the established safety and effectiveness of albuterol tablets in pediatric patients 6 years of age and older; and one clinical trial that provides evidence of the safety of albuterol extended-release tablets in pediatric patients aged 6 to 12 years. The recommended dose of albuterol extended-release tablets in the pediatric population is based upon the recommended pediatric dosing of albuterol tablets and pharmacokinetic studies in adults showing albuterol extended-release tablets to have similar peak albuterol levels (i.e. Cmax) and exposure (i.e. AUC) as albuterol tablets administered every 6 hours at one-half of the albuterol extended-release tablets dose.

Safety and effectiveness in pediatric patients below the age of 6 years for albuterol extended-release tablets and albuterol tablets have not been established.

ADVERSE REACTIONS

The adverse reactions to albuterol are similar in nature to those of other sympathomimetic agents.

Albuterol Tablets Adverse Experience Incidence (% of patients) in Adults and Children 6 Years of Age and Older

Adverse Event | Percent Incidence
Central nervous system
Nervousness | 20
Tremor | 20
Headache | 7
Dizziness | 2
Weakness | 2
Sleeplessness | 2
Irritability | < 1
Drowsiness | < 1
Restlessness | < 1
Cardiovascular
Palpitations | 5
Tachycardia | 5
Flushing | < 1
Chest discomfort | < 1
Musculoskeletal
Muscle cramps | 3
Gastrointestinal
Nausea | 2
Genitourinary
Difficulty in micturition | < 1

Albuterol Extended-release Tablets Incidence of Adverse Reactions (% of Patients) in a 1-week Clinical Trials*

Adverse Event | Albuterol Extended-release; Tablets (4 mg every 12; hours) | Albuterol Tablets (2 mg every 6 hours)
Nausea | 4 | 4
Nervousness | 2 | 6
Vomiting | 2 | 4
Somnolence | 2 | 2
*This table includes adverse reactions considered to be possibly or probably treatment related in 1-week clinical trial comparing a 4 mg albuterol extended-release tablet administered every 12 hours to a 2 mg albuterol tablet administered every 6 hours.

Although not reported for albuterol extended-release tablets in the above study, there have been reports of tremor in other trials. When all clinical experience is considered, the incidence of tremor is approximately the same as that seen with albuterol tablets.

A placebo-controlled trial of 4 weeks duration in 157 mild-to-moderate asthmatic children aged 6 to 12 years, demonstrated the safety of escalating doses of albuterol extended-release tablets. In this study, the starting dose of albuterol extended-release tablets was 4 mg twice daily. Patients were advanced to a maximum of 12 mg albuterol extended-release tablets twice daily by the investigator, based on patient tolerance and response. Only one of the 79 children treated with albuterol extended-release tablets was advanced to the maximum daily dose of 12 mg twice daily. The following treatment-related adverse events occurred in more than 5% of treated patients and were greater in albuterol extended-release tablets patients when compared to placebo:

Incidence of Adverse Events (% of Patients) in a 4-Week Placebo-Controlled Trial in 157 Children 6 to 12 Years of Age

Adverse Event | Albuterol Extended-release; Tablets % | Placebo %
Headache | 22 | 9
Nervousness | 13 | 6
Insomnia | 11 | 5
Tremor | 10 | 1
Palpitation | 8 | 1
Tachycardia | 8 | 1

Other adverse events were noted in 5% or fewer patients, or had equal or greater rates of occurrence in placebo patients than in albuterol extended-release tablets patients.

Cases of urticaria, angioedema, rash, bronchospasm, oropharyngeal edema and arrhytmias (including atrial fibrillation, supraventricular tachycardia, and extrasystoles) have been reported after the use of albuterol tablets.

In addition to those adverse reactions reported above, albuterol, like other sympathomimetic agents, can cause adverse reactions such as angina, central nervous system stimulation, drying or irritation of the oropharynx, hypertension, unusual taste, and vertigo.

The reactions are generally transient in nature, and it is usually not necessary to discontinue treatment with albuterol tablets. In selected cases, however, dosage may be reduced temporarily; after the reaction has subsided, dosage should be increased in small increments to the optimal dosage.

To report SUSPECTED ADVERSE REACTIONS, contact Amneal Pharmaceuticals at 1-877-835-5472 or FDA at 1-800-FDA-1088 or www.fda.gov/medwatch.

OVERDOSAGE

The expected symptoms with overdosage are those of excessive beta-adrenergic stimulation and/or occurrence or exaggeration of any of the symptoms listed under ADVERSE REACTIONS, e.g., angina, hypertension tachycardia with rates up to 200 beats per minute, nervousness, headache, tremor, dry mouth, palpitation, nausea, dizziness, and insomnia. In addition, seizures, hypotension, arrhythmias, fatigue, malaise and hypokalemia may also occur. As with all sympathomimetic medications, cardiac arrest and even death may be associated with abuse of albuterol tablets. Treatment consists of discontinuation of albuterol tablets together with appropriate symptomatic therapy. The judicious use of a cardioselective beta-receptor blocker may be considered, bearing in mind that such medication can produce bronchospasm. There is insufficient evidence to determine if dialysis is beneficial for overdosage of albuterol tablets.

The oral median lethal dose of albuterol sulfate in mice is greater than 2000 mg/kg (approximately 250 times the maximum recommended daily oral dose for adults on an mg/m^2 basis, and approximately 200 times the maximum recommended daily oral dose for children on an mg/m^2 basis). In mature rats, the subcutaneous (sc) median lethal dose of albuterol sulfate is approximately 450 mg/kg (approximately 110 times the maximum recommended daily oral dose for adults on an mg/m^2 basis, and approximately 90 times the maximum recommended daily oral dose for children on an mg/m^2 basis). In small young rats, the subcutaneous median lethal dose is approximately 2000 mg/kg (approximately 510 times the maximum recommended daily oral dose for adults on an mg/m^2 basis, and approximately 400 times the maximum recommended daily oral dose for children on an mg/m^2 basis).

DOSAGE AND ADMINISTRATION

The following dosages of albuterol tablets, USP are expressed in terms of albuterol base.

Usual Dosage

Pediatric Patients 6 to 12 Years of Age: For pediatric patients 6 to 12 years of age, the usual dosage is 2 mg three or four times a day.

Adults and Pediatric Patients Over 12 Years of Age: For adults and pediatric patients over 12 years of age, the usual starting dosage is 2 or 4 mg three or four times a day.

Dosage Adjustment

Pediatric Patients 6 to 12 Years of Age Who Fail to Respond to the Initial Starting Dosage of 2 mg Four Times a Day: For pediatric patients from 6 to 12 years of age who fail to respond to the initial starting dosage of 2 mg four times a day, the dosage may be cautiously increased stepwise, but not to exceed 24 mg/day (given in divided doses).

Adults and Pediatric Patients Over 12 Years of Age: For adults and pediatric patients over 12 years of age, a dosage above 4 mg four times a day should be used only when the patient fails to respond to lower dose. The dosage should be cautiously increased stepwise up to a maximum of 8 mg four times a day as tolerated if a favorable response does not occur with the 4 mg initial dosage.

Elderly Patients and Those Sensitive to Beta-adrenergic Stimulators: An initial dosage of 2 mg three or four times a day is recommended for elderly patients and for those with a history of unusual sensitivity to beta-adrenergic stimulators. If adequate bronchodilation is not obtained, dosage may be increased gradually as tolerated to as much as 8 mg three or four times a day.

The total daily dose should not exceed 24 mg per day in pediatric patients from 6 to 12 years of age and 32 mg in adults and pediatric patients over 12 years of age.

HOW SUPPLIED

Albuterol tablets, USP contain 2 mg or 4 mg of albuterol as 2.4 mg or 4.8 mg of albuterol sulfate, USP respectively.

Albuterol Tablets USP, 2 mg are supplied as white, round shaped, uncoated tablets, free from physical defects, debossed with “AA” and “91” on either side of score line and plain on other side.

They are available as follows:

Bottles of 100: NDC 69238-1344-1

Bottles of 500: NDC 69238-1344-5

Albuterol Tablets USP, 4 mg are supplied as white, round shaped, uncoated tablets, free from physical defects, debossed with “AA” and “90” on either side of score line and plain on other side.

They are available as follows:

Bottles of 100: NDC 69238-1345-1

Bottles of 500: NDC 69238-1345-5

Store at 20° to 25°C (68° to 77°F) [see USP Controlled Room Temperature].

Protect from light.

Dispense in a tight, light-resistant container as defined in the USP using a child-resistant closure. Keep this and all drugs out of the reach of children.

Manufactured by:
Amneal Pharmaceuticals Pvt. Ltd.
Oral Solid Dosage Unit
Ahmedabad 382213, INDIA

Distributed by:
Amneal Pharmaceuticals LLC
Bridgewater, NJ 08807

Rev. 10-2024-01

PRINCIPAL DISPLAY PANEL

NDC 69238-1344-1

Albuterol Tablets USP, 2 mg

Rx only

100 Tablets

Amneal Pharmaceuticals LLC

NDC 69238-1345-1

Albuterol Tablets USP, 4 mg

Rx only

100 Tablets

Amneal Pharmaceuticals LLC